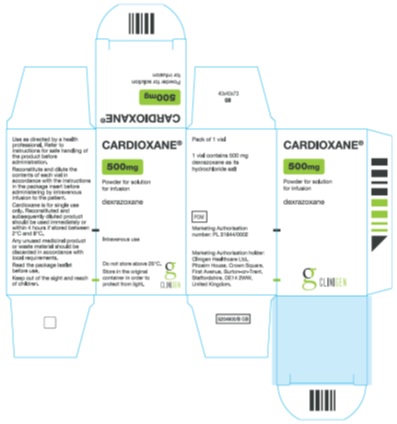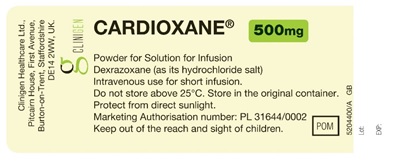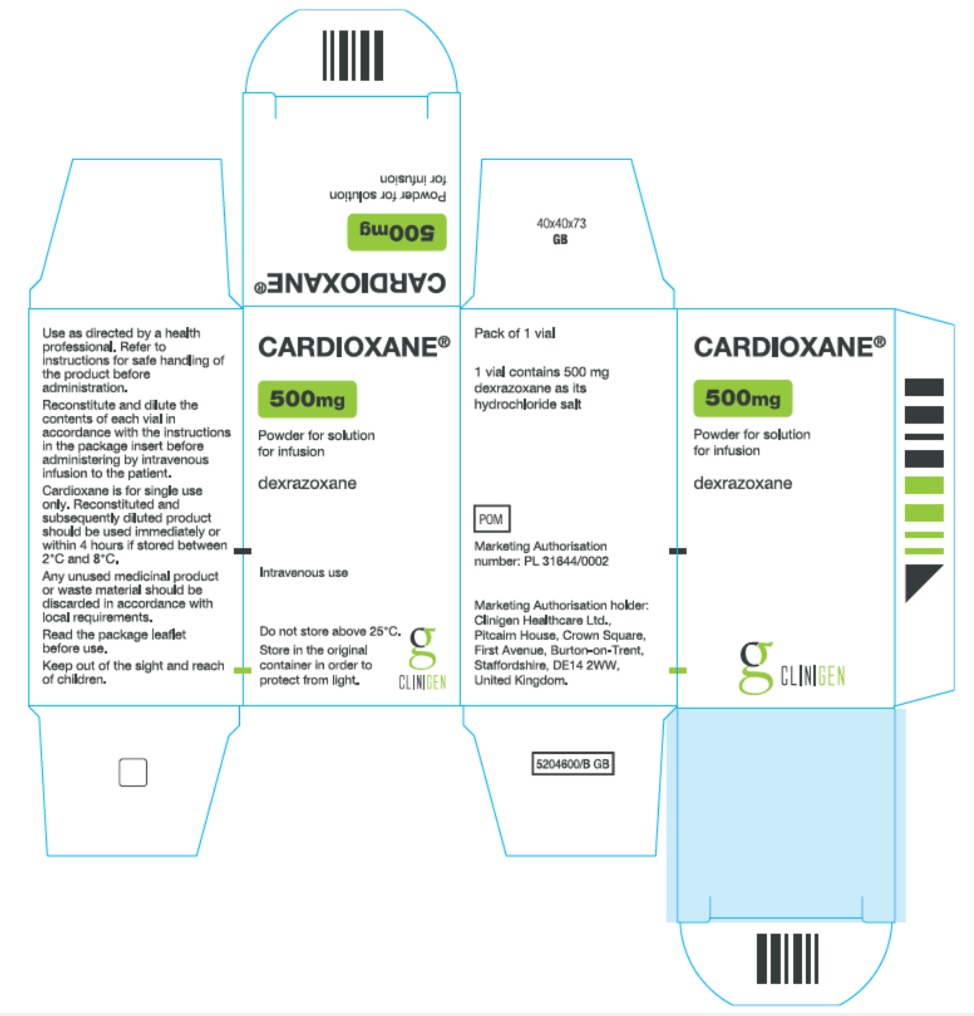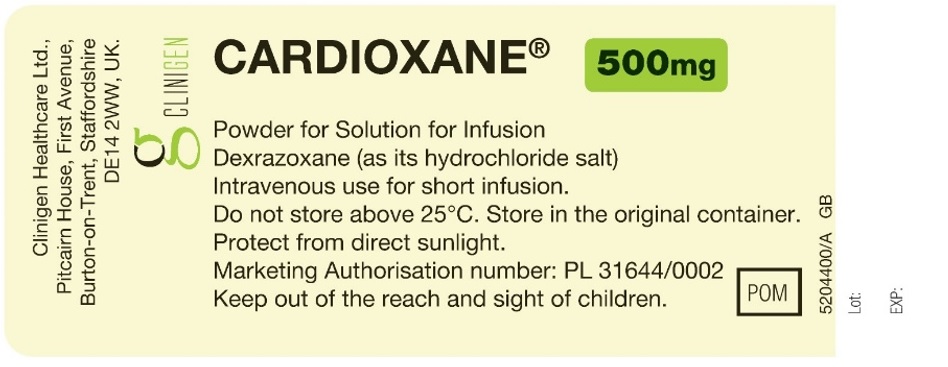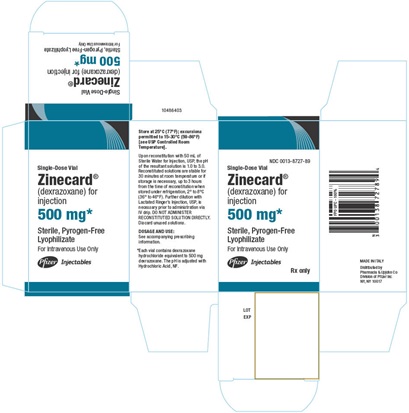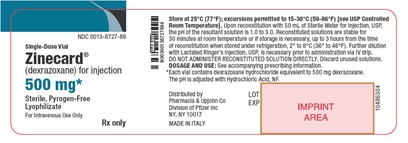 DRUG LABEL: Cardioxane
NDC: 76310-002 | Form: INJECTION, POWDER, FOR SOLUTION
Manufacturer: Clinigen Healthcare Ltd
Category: prescription | Type: HUMAN PRESCRIPTION DRUG LABEL
Date: 20170712

ACTIVE INGREDIENTS: DEXRAZOXANE HYDROCHLORIDE 500 mg/1 1
INACTIVE INGREDIENTS: HYDROCHLORIC ACID

Cardioxane 500 mg Powder for Solution for Infusion

IMPORTANT DRUG INFORMATION

Subject: Temporary Importation of Cardioxane 500 mg Powder for Solution for Infusion (dexrazoxane hydrochloride) to address drug shortage issues

Dear Healthcare Professional,

Important Reconstitution Note for Medication Error Prevention:

Prescribers and pharmacists must be alert to the differences between the FDA-approved dexrazoxane products and Cardioxane’s presentation and reconstitution and dilution instructions in order to prevent medication errors. Appropriate quality assurance measures should be enacted to reduce the risk of medication errors. See comparison table below for more information.

Cardioxane has a different vial capacity than FDA-approved dexrazoxane products, and, therefore must be reconstituted with a different volume of Water for Injection. Cardioxane 500 mg Powder for Solution for Infusion is provided in a vial with a capacity of 25 mL. To reconstitute, add 25 mL Water for Injection (USP) to the vial. The concentration of the resulting reconstitution solution will be 20 mg/mL – this solution should not be stored and must be further diluted before administration to the patient. Further dilute the reconstitution solution with Lactated Ringer's Injection, USP to a final concentration between 1.3 and 3 mg/mL. The diluted infusion solution should be used immediately or stored for a maximum of 4 hours under refrigeration.

Due to the current critical shortage of Dexrazoxane for Injection, 250 mg/vial and 500 mg/vial in the United States (U.S.) market, Clinigen Healthcare Ltd is coordinating with the U.S. Food and Drug Administration (FDA) to increase the availability of Dexrazoxane for Injection 500 mg/vial.

Clinigen Healthcare Ltd has initiated temporary importation into the U.S. of Cardioxane 500 mg Powder for Solution for Infusion (dexrazoxane hydrochloride), a non-FDA approved product, to help alleviate the shortage. The Cardioxane 500 mg Powder for Solution for Infusion was manufactured by Cenexi – Laboratoires Thissen S.A. in its FDA-inspected facility in Braine l’Alleud, Belgium and is licensed for sale in the United Kingdom. Clinigen Healthcare Ltd’s distributor for Cardioxane in the US is Cumberland Pharmaceuticals Inc.

At this time, no other entities except Clinigen Healthcare Ltd and its distributor Cumberland Pharmaceutical Inc. are authorized by the FDA to import or distribute Cardioxane 500 mg Powder for Solution for Infusion in the U.S. This does not constitute an FDA approval for the Cardioxane 500 mg Powder for Solution for Infusion being distributed in the U.S.

Cardioxane 500 mg Powder for Solution for Infusion contains the same active substance, dexrazoxane hydrochloride, as FDA-approved Zinecard. It is available as 500 mg/vial (no 250 mg/vial presentation is available). It is a clinically acceptable substitute for the out of stock U.S. Dexrazoxane for Injection products. Cardioxane is available only by prescription in the U.S.

In the U.S., the labelling for Dexrazoxane Injection (Zinecard) includes the following indication: ZINECARD is indicated for reducing the incidence and severity of cardiomyopathy associated with doxorubicin administration in women with metastatic breast cancer who have received a cumulative doxorubicin dose of 300 mg/m^2 and who will continue to receive doxorubicin therapy to maintain tumor control. Do not use with the initiation of doxorubicin therapy.

Comparison of Cardioxane and FDA-approved Zinecard

It is important to note the following differences between the U.S. FDA approved Dexrazoxane for Injection products and Cardioxane (a comparison of the carton and vial labels is appended to this letter for reference):

Dexrazoxane for Injection (U.S.) | Cardioxane (UK) | Action to Take
Packaged with complete prescribing Information. | Packaged with a Patient Information Leaflet, with information for Healthcare Professionals – this does not provide complete information for use. | Please refer to the package insert for the U.S. FDA approved Zinecard (dexrazoxane) for Injection for full prescribing information.
Presentation 250 mg/vial and 500 mg/vial. | Presentation 500 mg/vial only. | Prescribers and pharmacists must be alert to this difference in presentation in order to prevent medication errors.
Zinecard 500 mg/vial is reconstituted with 50 mL of Sterile Water for Injection USP.; Reconstituted solution has a concentration of 10 mg/mL. | Cardioxane 500mg/vial is reconstituted with 25 mL of Water for Injection.; Reconstituted solution has a concentration of 20 mg/mL. | The Cardioxane reconstituted solution will have a concentration of 20 mg/mL, this must be considered when further diluting to give an infusion solution.; Prescribers and pharmacists must be alert to this difference in order to prevent medication errors.
Following reconstitution with Sterile Water for Injection, USP, Zinecard is stable for 30 minutes at room temperature or if storage is necessary, up to 3 hours from the time of reconstitution when stored under refrigeration, 2° to 8°C (36° to 46°F). | No storage recommendations are given for the reconstituted solution – it should be immediately diluted for infusion. | Use the reconstituted solution immediately.
The reconstituted solution is diluted further with Lactated Ringer's Injection, USP to a concentration of 1.3 mg/mL to 3 mg/mL in intravenous infusion bags for intravenous infusion. | The reconstituted solution is diluted further with Lactated Ringer’s Injection or Sodium Lactate 0.16 M to a concentration between 4 mg/mL to 10 mg/mL. | Recall that the reconstitution solution will have a concentration of 20 mg/mL.; Follow the instructions given within the Zinecard Prescribing Information – dilute with Lactated Ringer’s Injection USP to 1.3 mg/mL to 3 mg/mL in intravenous infusion bags for intravenous infusion.
The diluted infusion solutions are stable for one hour at room temperature or if storage is necessary, up to 4 hours when stored under refrigeration, 2° to 8°C (36° to 46°F). | Reconstituted and subsequently diluted product should be used immediately or within 4 hours if stored between 2°C and 8°C. | The diluted infusion solution should be used immediately or stored for a maximum of 4 hours under refrigeration, 2° to 8°C (36° to 46°F).

Please note that no barcode appears on the carton for Cardioxane 500 mg Powder for Solution for Infusion, therefore it will not be appropriately recognized by scanning systems used in the United States. Alternative procedures should be followed to assure that the correct drug product is being used and administered to individual patients.

To order Cardioxane 500 mg Powder for Solution for Infusion, please contact the distributor Cumberland Pharmaceuticals Inc., at 615-255-0068, or by email at jherman@cumberlandpharma.com.

To report adverse events or other safety-related information, including medication errors to Clinigen Healthcare, you may complete the available form at http://www.clinigengroup.com/node/99 and send via email to patientsafety@clinigengroup.com or fax to 1-800-861-9362. Adverse events and medication errors, or quality problems experienced with the use of this product may also be reported to the FDA’s MedWatch Adverse Event Reporting Program either online, or regular mail, or by fax:

- Complete and submit the report Online: www.fda.gov/medwatch/report.htm
- Regular mail or Fax: Download form www.fda.gov/MedWatch/getforms.htm or call 1-800-332-1088 to request a reporting form, then complete and return to the address on the pre-addressed form, or submit by fax to 1-800-FDA-0178.

We urge you to contact our Medical Information Department at toll-free 888-758-7954 during office hours (Monday to Friday, 8am to 5:30pm Eastern Time), or at 913-339-8424 out of office hours, or email clinigenUS@medinfodept.com, if you have any questions about the information contained in this letter or the safe and effective use of Cardioxane 500 mg Powder for Solution for Infusion.

Comparison of Carton and Vial Labels (Zinecard and Cardioxane 500 mg Powder for Solution for Infusion)

Item | Zinecard (US) | Cardioxane 500 mg Powder for Solution for Infusion
Carton Label | Principal Panel; NDC 0013-8727-89; Single-Dose Vial; Zinecard®; (dexrazoxane) for; injection; 500 mg*; Sterile, Pyrogen-Free; Lyophilizate; For Intravenous Use Only; Pfizer Injectables; Rx only; Side Panel 1; Store at 25°C (77°F); excursions permitted to 15-30°C (59-86°F) [see USP Controlled Room Temperature].; Upon reconstitution with 50 mL of Sterile Water for Injection, USP, the pH of the resultant solution is 1.0 to 3.0. Reconstituted solutions are stable for 30 minutes at room temperature or if storage is necessary, up to 3 hours from the time of reconstitution when stored under refrigeration, 2° to 8°C (36° to 46°F). Further dilution with Lactated Ringer’s, USP, is necessary prior to administration via IV drop. DO NOT ADMINISTER RECONSTITUTED SOLUTION DIRECTLY. Discard unused solutions.; DOSAGE AND USE: See accompanying prescribing information.; *Each vial contains dexrazoxane hydrochloride equivalent to 500 mg dexrazoxane. The pH is adjusted with Hydrochloric Acid, NF.; Side Panel 2; Barcode; MADE IN ITALY; Distributed by; Pharmacia & Upjohn Co; Division of Pfizer Inc; NY, NY 10017 | Principal Panel; Cardioxane® 500mg; Powder for solution for infusion; Dexrazoxane; Intravenous use; Do not store above 25°C.; Store in the original container in order to protect from light.; Side Panel 1; Use as directed by a health professional. Refer to instructions for safe handling of product before administration.; Reconstitute and dilute the contents of each vial in accordance with the instructions in the package insert before administering by intravenous infusion to the patient.; Cardioxane is for single use only. Reconstituted and subsequently diluted product should be used immediately or within 4 hours if stored between 2°C and 8°C.; Any unused medicinal product should be discarded in accordance with local requirements.; Read the package leaflet before use.; Keep out of the sight and reach of children.; Side Panel 2; Pack of 1 vial; 1 vial contains 500 mg dexrazoxane as its hydrochloride salt; POM; Marketing Authorisation number: PL 31644/0002; Marketing Authorisation holder: Clinigen Healthcare Ltd., Pitcairn House, Crown Square, First Avenue, Burton-on-Trent, Staffordshire, DE14 2WW, United Kingdom.
Carton Label Image

Item | Zinecard (US) | Cardioxane 500 mg Powder for Solution for Infusion
Vial Label | Principal Panel; NDC 0013-8727-89; Single-Dose Vial; Zinecard®; (dexrazoxane) for injection; 500 mg*; Sterile, Pyrogen-Free; Lyophilizate; For Intravenous Use Only; Rx only; Side Panel; Store at 25°C (77°F); excursions permitted to 15-30°C (59-86°F) [see USP Controlled Room Temperature]. Upon reconstitution with 50 mL of Sterile Water for Injection, USP, the pH of the resultant solution is 1.0 to 3.0. Reconstituted solutions are stable for 30 minutes at room temperature or if storage is necessary, up to 3 hours from the time of reconstitution when stored under refrigeration, 2° to 8°C (36° to 46° F). Further dilution with Lactated Ringer’s, USP, is necessary prior to administration via IV drop. DO NOT ADMINISTER RECONSTITUTED SOLUTION DIRECTLY. Discard unused solutions. DOSAGE AND USE: See accompanying prescribing information. *Each vial contains dexrazoxane hydrochloride equivalent to 500 mg dexrazoxane. The pH is adjusted with Hydrochloric Acid, NF.; Distributed by; Pharmacia & Upjohn Co; Division of Pfizer Inc; NY, NY 10017; MADE IN ITALY; LOT; EXP | Principal Panel; Cardioxane® 500 mg; Powder for Solution for Infusion; Dexrazoxane (as its hydrochloride salt); Intravenous use for short infusion.; Do not store above 25°C. Store in the original container.; Protect from direct sunlight.; Marketing Authorisation number: PL 31644/0002; Keep out of the reach and sight of children.; POM; Side Panel; Clinigen Healthcare Ltd.; Pitcairn House, First Avenue,; Burton-on-Trent, Staffordshire; DE14 2WW, UK.
Vial Label Image

PACKAGE LABEL

Carton

Label